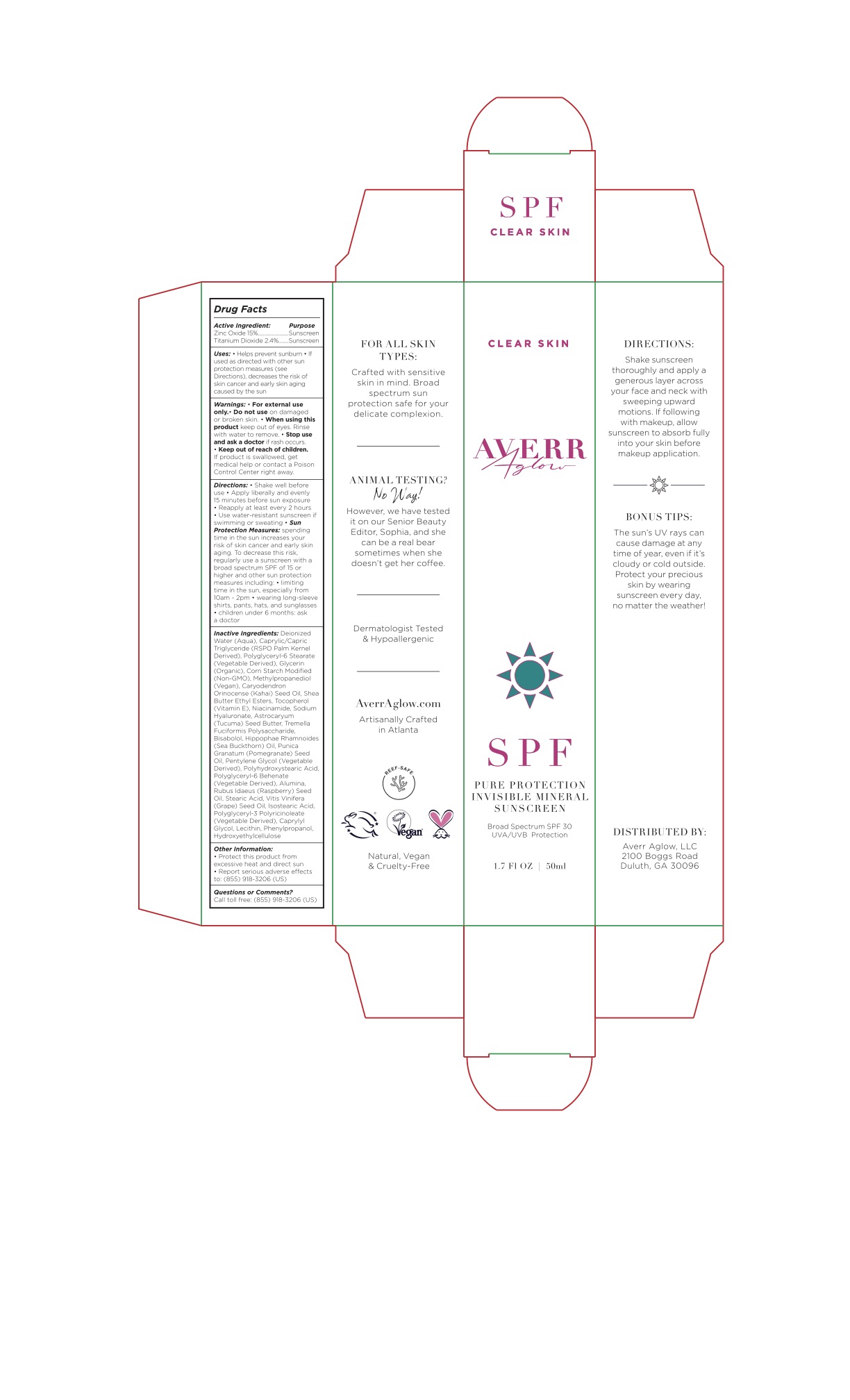 DRUG LABEL: Averr Aglow Pure Protection Invisible Mineral Sunscreen Broad Spectrum SPF 30
NDC: 81664-001 | Form: LOTION
Manufacturer: Averr Aglow LLC
Category: otc | Type: HUMAN OTC DRUG LABEL
Date: 20210322

ACTIVE INGREDIENTS: ZINC OXIDE 166.5 mg/1 mL; TITANIUM DIOXIDE 26.64 mg/1 mL
INACTIVE INGREDIENTS: NIACINAMIDE; HYALURONATE SODIUM; CAPRYLIC/CAPRIC MONO/DI-GLYCERIDES; ISOSTEARIC ACID; STEARIC ACID; LECITHIN, SUNFLOWER; TOCOPHEROL; POMEGRANATE SEED OIL; SHEA BUTTER ETHYL ESTERS; ASTROCARYUM VULGARE KERNEL OIL; POLYGLYCERYL-6 STEARATE; POLYGLYCERYL-6 BEHENATE; CAPRYLYL GLYCOL; .ALPHA.-BISABOLOL, (+)-; WATER; PENTYLENE GLYCOL; HYDROXYETHYL CELLULOSE, UNSPECIFIED; CARYODENDRON ORINOCENSE WHOLE; GLYCERIN; TREMELLA FUCIFORMIS WHOLE; METHYLPROPANEDIOL; HIPPOPHAE RHAMNOIDES WHOLE; GRAPE SEED OIL; RASPBERRY SEED OIL; PHENYLPROPANOL; MODIFIED CORN STARCH (1-OCTENYL SUCCINIC ANHYDRIDE); POLYHYDROXYSTEARIC ACID (2300 MW)

Active Ingredient[s]

Zinc Oxide 15%

Titanium Dioxide 2.4%

Purpose

Sunscreen

Uses

- Helps prevent sunburn
- If used as directed with other sun protection measures (see Directions), decreases the risk of skin cancer and early skin aging caused by the sun

Warnings

For external use only.

Warnings

Do not use on damaged or broken skin

Warnings

When using this product keep out of eyes. Rinse with water to remove

Warnings

Stop use and ask a doctor if rash occurs

Warnings

Keep out of reach of children. If product is swallowed, get medical help or contact a Poison Control Center right away.

Directions

- Shake well before use
- Apply liberally and evenly 15 minutes before sun exposure
- Reapply at least every 2 hours
- Use water-resistant sunscreen if swimming or sweating
- Sun Protection Measures: spending time in the sun increases your risk of skin cancer and early skin aging. To decrease this risk, regularly use a sunscreen with a broad spectrum SPF of 15 or higher and other sun protection measures including:
  1. limiting time in the sun, especially from 10 a.m. - 2 p.m.
  2. wearing long-sleeve shirts, pants, hats, and sunglasses
  3. children under 6 months: Ask a doctor

Inactive Ingredients

Deionized Water (Aqua), Caprylic/Capric Triglyceride (RSPO Palm Kernel Derived), Polyglyceryl-6 Stearate (Vegetable Derived), Glycerin (Organic), Corn Starch Modified (non-GMO), Methylpropanediol, Caryodendron Orinocense (Kahai) Seed Oil, Shea Butter Ethyl Esters, Tocopherol (Vitamin E), Niacinamide, Sodium Hyaluronate, Astrocaryum (Tucuma) Seed Butter, Tremella Fuciformis Polysaccharide, Bisabolol, Hippophae Rhamnoides (Sea Buckthorn) Oil, Punica Granatum (Pomegranate) Seed Oil, Pentylene Glycol (Vegetable Derived), Polyhydroxystearic Acid, Polyglyceryl-6 Behenate (Vegetable Derived), Alumina, Rubus Idaeus (Raspberry) Seed Oil, Stearic Acid, Vitis Vinifera (Grape) Seed Oil, Isostearic Acid, Polyglyceryl-3 Polyricinoleate (Vegetable Derived), Caprylyl Glycol, Lecithin, Phenylpropanol, Hydroxyethylcellulose

Other Information

Protect this product from excessive heat and direct sun. Report serious adverse effects to: (855) 918-3206 (US)

Questions or Comments?

Call toll free: (855) 918-3206 (US)